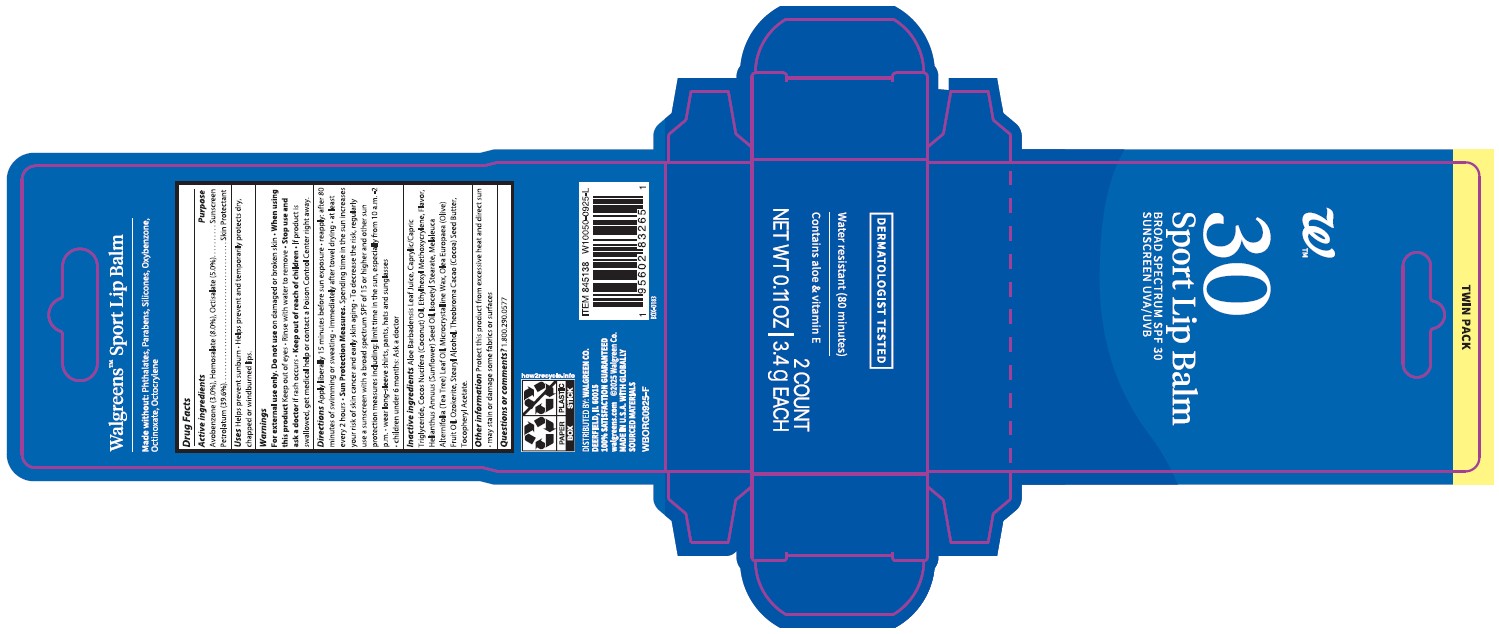 DRUG LABEL: Walgreens Sport Lip Balm
NDC: 0363-9789 | Form: STICK
Manufacturer: Walgreens
Category: otc | Type: HUMAN OTC DRUG LABEL
Date: 20251121

ACTIVE INGREDIENTS: PETROLATUM 396 mg/1 g; AVOBENZONE 30 mg/1 g; HOMOSALATE 80 mg/1 g; OCTISALATE 50 mg/1 g
INACTIVE INGREDIENTS: WHITE WAX 165 mg/1 g; MICROCRYSTALLINE WAX 11 mg/1 g

Drug Facts

Active ingredient

Avobenzone 3.0%, Homosalate 8.0%, Octisalate 5.0%

Petrolatum, 39.6%

Purpose

Sunscreen

Skin Protectant

Keep Out of Reach of Children

If product is swallowed, get medical help or contact a Poison Control Center right away.

Uses

Helps prevent sunburn. Helps prevent and temporarily protects dry, chapped or windburned lips.

Warnings

For external use only. Do not use on damaged or broken skin. When using this product: Keep out of eyes. Risnse with water to remove. Stop use and ask a doctor if ·rash occurs·

Directions

Apply liberally 15 minutes before sun exposure. Reapply; after 80 minutes of swimming or sweating. Immediately after towel drying.at least every 2 hours. Sun Protection Measures: Spending time in the sun increases your risk of skin cancer and early skin aging. To decrease the risk, regularly use a sunscreen with a broad spectrum SPF of 15 or higher and other sun protection measures including: limit time in the sun, especially from 10 a.m. – 2 p.m. wear long sleeve shirts, pants, hats, and sunglasses. Children under 6 months: Ask a doctor.

Inactive Ingredients

Aloe Barbadensis Leaf Juice, Caprylic/Capric Triglyceride, Cocos Nucifera (Coconut) Oil, Ethylhexyl Methoxycrylene, Flavor, Helianthus Annuus (Sunflower) Seed Oil, Isocetyl Stearate, Melaleuca Alternifolia (Tea Tree) Leaf Oil, Microcrystalline Wax, Olea Europaea (Olive) Fruit Oil, Ozokerite, Stearyl Alcohol, Theobroma Cacao (Cocoa) Seed Butter, Butyrospermum Parkii (Shea Butter), Tocopheryl Acetate.

Questions

1-800-290-0577